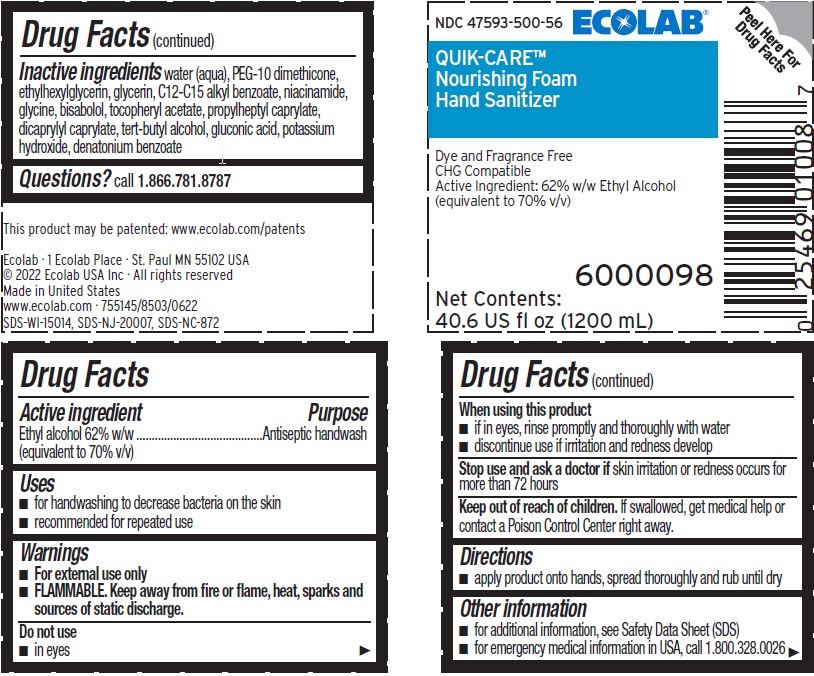 DRUG LABEL: Quik-Care Nourishing Foam Hand Sanitizer
NDC: 47593-500 | Form: SOLUTION
Manufacturer: Ecolab Inc.
Category: otc | Type: HUMAN OTC DRUG LABEL
Date: 20260102

ACTIVE INGREDIENTS: ALCOHOL 70 mL/100 mL
INACTIVE INGREDIENTS: WATER; PEG-10 DIMETHICONE (600 CST); ETHYLHEXYLGLYCERIN; GLYCERIN; ALKYL (C12-15) BENZOATE; NIACINAMIDE; GLYCINE; .ALPHA.-BISABOLOL, (+/-)-; .ALPHA.-TOCOPHEROL ACETATE; PROPYLHEPTYL CAPRYLATE; DICAPRYLYL CARBONATE; TERT-BUTYL ALCOHOL; GLUCONIC ACID; POTASSIUM HYDROXIDE; DENATONIUM BENZOATE

Drug Facts

Active ingredient

Ethyl alcohol 62% w/w (equivalent to 70% v/v)

Purpose

Antiseptic handwash

Uses

- For handwashing to decrease bacteria on the skin
- Recommended for repeated use

Warnings

- For external use only
- FLAMMABLE, keep away from fire or flame, heat, sparks and sources of static discharge.

Do not use

- In eyes

When using this product

- If in eyes, rinse promptly and thoroughly with water
- Discontinue use if irritation and redness develop

Stop use and ask a doctor if

- Skin irritation or redness occurs for more than 72 hours

Keep out of reach of children. If swallowed, get medical help or contact a Poison Control Center right away.

Directions

- Apply product onto hands, spread throughly and rub until dry

Other information

- for additional information, see Safety Data Sheet (MSDS)
- for emergency medical information in USA, call 1 800 328 0026

INACTIVE INGREDIENT

Inactive ingredients water (aqua), PEG-10 dimethicone, ethylhexylglycerin, glycerin, C12-C15 alkyl benzoate, niacinamide, glycine, bisabolol, tocopheryl acetate, propylheptyl caprylate, dicaprylyl caprylate, tert-butyl alcohol, gluconic acid, potassium hydroxide, denatonium benzoate

Questions? call 1 866 781 8787

Principal Display Panel and Representative Label

ECOLAB®

NDC 47593-500-56

QUIK-CARE®

Nourishing Foam

Hand Sanitizer

Dye and Fragrance Free

CHG Compatible

Active Ingredient: 62% Ethyl Alcohol

(equivalent to 70% v/v)

6000098

Net Contents: 40.6 US fl oz (1200 mL)

This product may be patented: www.ecolab.com/patents

Ecolab · 1 Ecolab Place · St. Paul MN 55102 USA

© 2022 Ecolab USA Inc · All rights reserved

Made in United States

www.ecolab.com · 755145/8503/0622

SDS-WI-15014, SDS-NJ-20007, SDS-NC-872